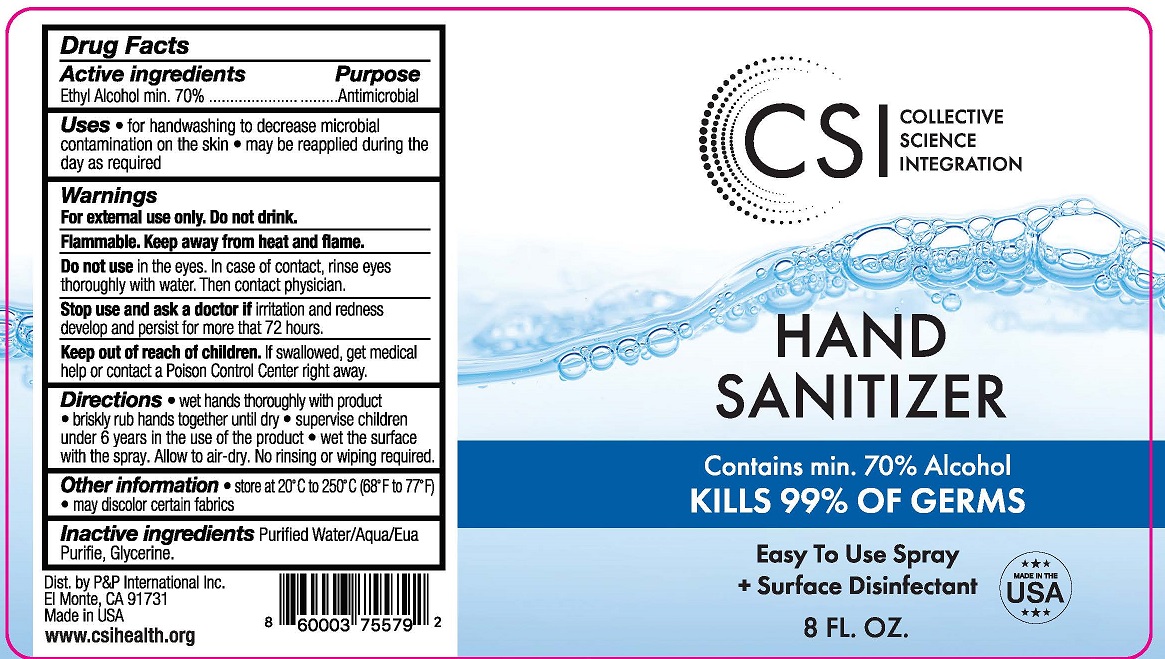 DRUG LABEL: HAND SANITIZER

NDC: 50518-307 | Form: SPRAY
Manufacturer: CUSTOM RESEARCH LABS INC
Category: otc | Type: HUMAN OTC DRUG LABEL
Date: 20220329

ACTIVE INGREDIENTS: ALCOHOL 70 mL/100 mL
INACTIVE INGREDIENTS: WATER; GLYCERIN; POWDERED CELLULOSE

CRL (as CMO) - CSI - HAND SANITIZER SPRAY - 70% ETHYL ALCOHOL (50518-307)

ACTIVE INGREDIENT

ETHYL ALCOHOL 70%

PURPOSE

ANTIMICROBIAL

USES

- FOR HANDWASHING TO DECREASE MICROBIAL CONTAMINATION ON THE SKIN
- MAY BE REAPPLIED DURING THE DAY AS REQUIRED

WARNINGS

FOR EXTERNAL USE ONLY. DO NOT DRINK.

FLAMMABLE, KEEP AWAY FROM FIRE AND FLAME.

DO NOT USE IN THE EYES. IN CASE OF CONTACT, RINSE EYES THOROUGHLY WITH WATER, THEN CONTACT PHYSICIAN.

STOP USE AND ASK A DOCTOR IF IRRITATION AND REDNESS DEVELOP AND PERSISTS FOR MORE THAN 72 HOURS

KEEP OUT OF REACH OF CHILDREN. IF SWALLOWED, GET MEDICAL HELP OR CONTACT A POISON CONTROL CENTER RIGHT AWAY.

DIRECTIONS

- WET HANDS THOROUGHLY WITH PRODUCT
- BRISKLY RUB HANDS TOGETHER UNTIL DRY
- SUPERVISE CHILDREN UNDER 6 YEARS IN THE USE OF PRODUCT
- WET THE SURFACE WITH THE SPRAY. ALLOW TO AIR DRY. NO RINSING OR WIPING REQUIRED.

OTHER INFORMATION

- STORE AT 20°C TO 25°C (68°F TO 77°F)

- MAY DISCOLOR SOME FABRICS

INACTIVE INGREDIENTS

PURIFIED WATER/AQUA/EAU PURIFIE, GLYCERIN